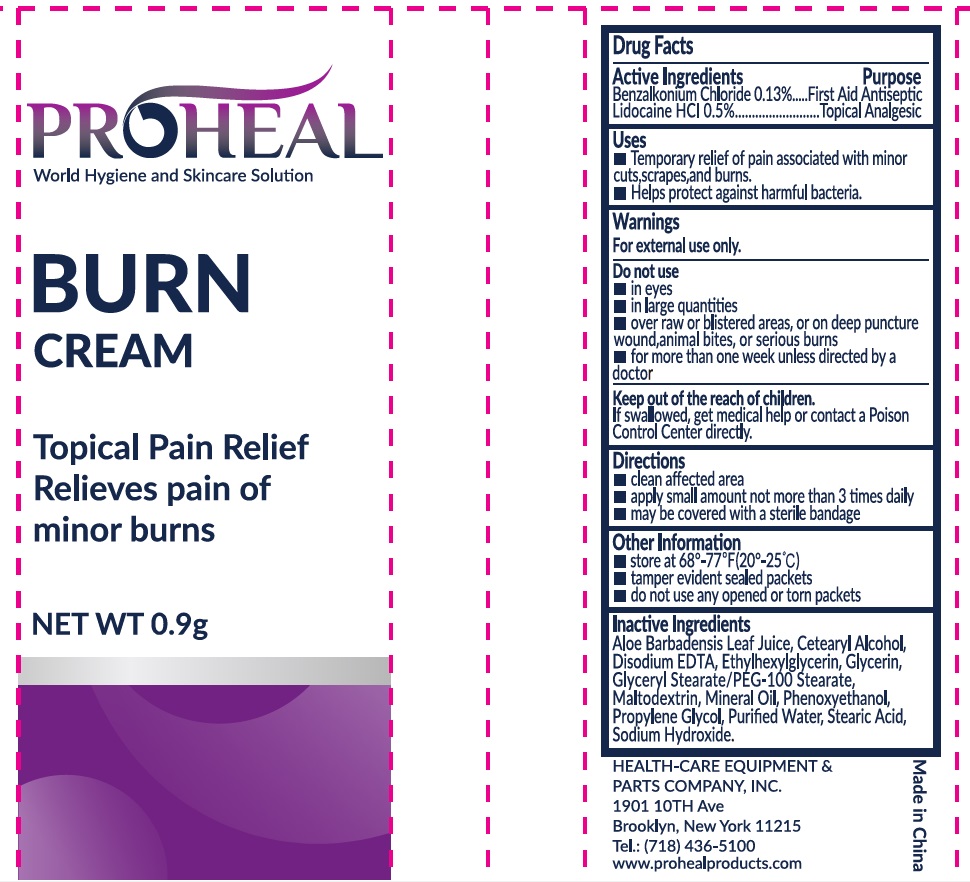 DRUG LABEL: PROHEAL BURN
NDC: 43473-066 | Form: CREAM
Manufacturer: Nantong Health & Beyond Hygienic Products Inc.
Category: otc | Type: HUMAN OTC DRUG LABEL
Date: 20250119

ACTIVE INGREDIENTS: LIDOCAINE HYDROCHLORIDE 0.5 g/100 g; BENZALKONIUM CHLORIDE 0.13 g/100 g
INACTIVE INGREDIENTS: WATER; ALOE VERA LEAF; CETOSTEARYL ALCOHOL; GLYCERIN; DISODIUM HEDTA; ETHYLHEXYLGLYCERIN; GLYCERYL STEARATE/PEG-100 STEARATE; MALTODEXTRIN; PHENOXYETHANOL; PROPYLENE GLYCOL; STEARIC ACID; MINERAL OIL; SODIUM HYDROXIDE

43473-066 PROHEAL burn cream

Active ingredient

Benzalkonium Chloride 0.13%

Lidocaine HCI 0.5%

Purpose

First Aid Antiseptic
Topical Analgesic

Uses

Temporary relief of pain associated with minor cuts, scrapes, and burns.
Helps protect against harmful bacteria.

Warnings

For external use only.

Do not use

- in eyes
- in large quantities
- over raw or blistered areas, or on deep puncture wounds, animal bites, or serious burns
- for more than one week unless directed by a doctor

Keep out of reach of children. If swallowed, get medical help or contact a Poison Control Center directly.

Directions

- clean affected area
- apply small amount not more than 3 times daily
- may be covered with a sterile bandage

Other Information

- store at 68-77F (20-25C)
- tamper evident sealed packets
- do not use any opened or torn packets

Inactive ingredients

Aloe Barbadensis Leaf Juice, Cetearyl Alcohol, Disodium EDTA, Ethylhexylglycerin, Glycerin, Glyceryl Stearate/PÉG-100 Stearate, Maltodextrin, Mineral Oil, Phenoxyethanol, Propylene Glycol, Purified Water, Stearic Acid, Sodium Hydroxide